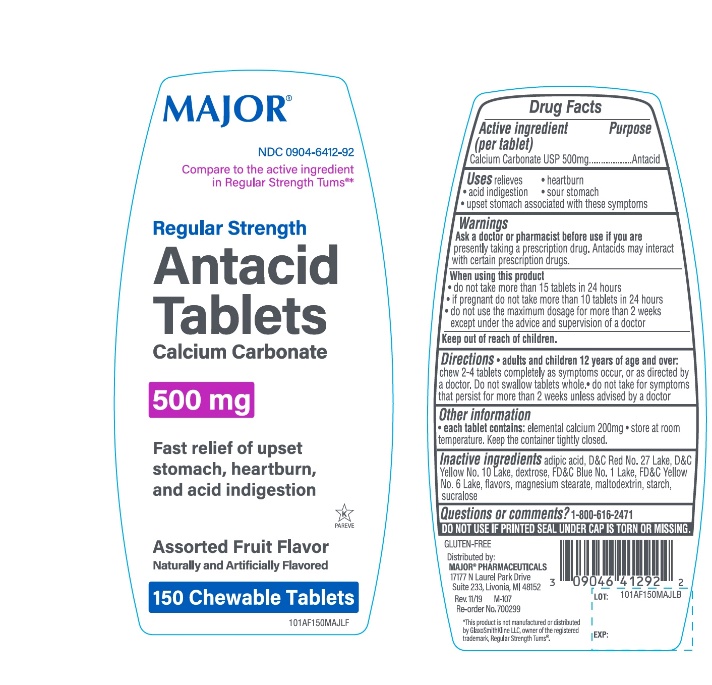 DRUG LABEL: Major Regular Strength

NDC: 0904-6412 | Form: TABLET, CHEWABLE
Manufacturer: Major Pharmaceuticals
Category: otc | Type: HUMAN OTC DRUG LABEL
Date: 20250919

ACTIVE INGREDIENTS: CALCIUM CARBONATE 500 mg/1 1
INACTIVE INGREDIENTS: D&C YELLOW NO. 10; DEXTROSE, UNSPECIFIED FORM; FD&C BLUE NO. 1; FD&C YELLOW NO. 6; MAGNESIUM STEARATE; MALTODEXTRIN; STARCH, CORN; SUCRALOSE; ADIPIC ACID; D&C RED NO. 27

Major Regular Strength Antacid 150 Chewable Tablets

Active ingredient

Calcium Carbonate USP 500mg

Purpose

Antacid

Uses

relieves:

• heartburn

• sour stomach

• acid indigestion

• upset stomach associated with these symptoms

Warnings

Ask a doctor or pharmacist before use if you are presentlytaking a prescription drug. Antacids may interact with certain prescription drugs.

When using this product

- do not take more than 15 tablets in 24 hours
- If pregnant do not take more than 10 tablets in 24 hours
- do not use the maximum dosage for more than 2 weeks except under the advice and supervision of a doctor.

Directions

- Adults and children 12 years of age and over:chew 2-4 tablets as symptoms occur, or as directed by a doctor.
- Do not swallow tablets whole,
- Do not take for symptoms that persist for more than 2 weeks unless advised by a doctor.

Other Information

- Each tablet contains: elemental calcium 200 mg
- Store at room temperature. Keep the container tightly closed

Safety sealed: Do not use if printed seal under cap is torn or missing.

Inactive ingredients

adipic acid, D&C Red No.27 lake, D&C Yellow No.10 lake, dextrose, FD&C Blue No.1 lake, FD&C Yellow No.6 lake, flavors, magnesium stearate, maltodextrin, starch, sucralose.

Package/Label Principal Display Panel

Compare to active ingredient in Regular Strength Tums®*

MAJOR®

NDC 0904-6412-92

Regular Strength

Antacid Tablets

Calcium Carbonate 500mg

Fast relief of upset stomach, heartburn, and acid indigestion

Assorted Fruit Flavor

Naturally & Artificially Flavored

150 Chewable Tablets

K PAREVE

GLUTEN- FREE

Distributed by: MAJOR®PHARMACEUTICALS

17177 N Laurel Park Drive, Suite 233

Livonia, MI 48152, USA

M-107 REV. 11/19

*This product is not manufactured or distributed by GlaxoSmithKline LLC, owner of the registered trademark, Regular Strength Tums®.